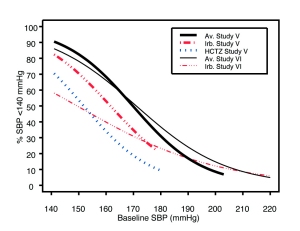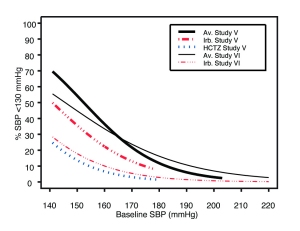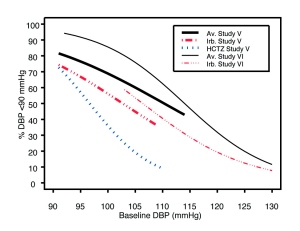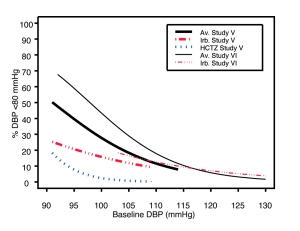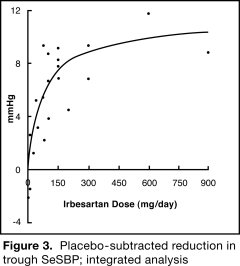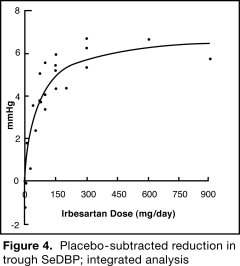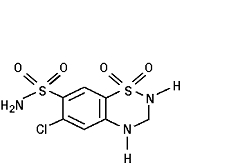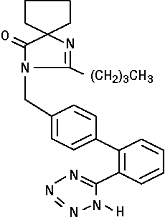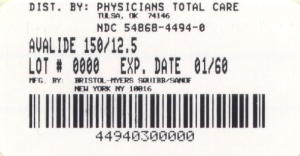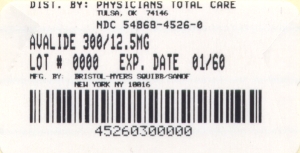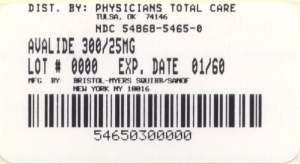 DRUG LABEL: Avalide
NDC: 54868-4494 | Form: TABLET
Manufacturer: Physicians Total Care, Inc.
Category: prescription | Type: HUMAN PRESCRIPTION DRUG LABEL
Date: 20100119

ACTIVE INGREDIENTS: IRBESARTAN 150 mg/1 1; HYDROCHLOROTHIAZIDE 12.5 mg/1 1
INACTIVE INGREDIENTS: LACTOSE MONOHYDRATE; CELLULOSE, MICROCRYSTALLINE; STARCH, CORN; CROSCARMELLOSE SODIUM; FERRIC OXIDE RED; FERRIC OXIDE YELLOW; SILICON DIOXIDE; MAGNESIUM STEARATE

HIGHLIGHTS OF PRESCRIBING INFORMATION

These highlights do not include all the information needed to use AVALIDE safely and effectively. See full prescribing information for AVALIDE. AVALIDE (irbesartan and hydrochlorothiazide) tablet for oral use AVALIDE (irbesartan and hydrochlorothiazide) tablet, film coated for oral use Initial U.S. Approval: 1997

WARNING: USE IN PREGNANCY

See full prescribing information for complete boxed warning.

When pregnancy is detected, discontinue AVALIDE as soon as possible. When used in pregnancy during the second and third trimesters, drugs that act directly on the renin-angiotensin system can cause injury and even death to the developing fetus. (5.1)

1 INDICATIONS AND USAGE

AVALIDE is a combination of irbesartan, an angiotensin II receptor antagonist, and hydrochlorothiazide, a thiazide diuretic, indicated for hypertension:

- In patients not adequately controlled with monotherapy (1)
- As initial therapy in patients likely to need multiple drugs to achieve their blood pressure goals (1).

2 DOSAGE AND ADMINISTRATION

General Considerations

- Maximum effects within 2 to 4 weeks after dose change (2.1).
- Renal impairment: Not recommended for patients with severe renal impairment (creatinine clearance less than 30 mL/min) (2.1, 5.8).

Hypertension

- Not controlled on monotherapy: Initiate with 150/12.5 mg. Titrate to 300/12.5 mg then 300/25 mg if needed. One tablet daily (2.2).
- Replacement therapy: May be substituted for titrated components (2.3).
- Initial therapy: Initiate with 150/12.5 mg once daily for 1 to 2 weeks and titrate as needed up to maximum of 300/25 mg once daily (2.4).

3 DOSAGE FORMS AND STRENGTHS

- 150 mg irbesartan/12.5 mg hydrochlorothiazide tablets (3)
- 300 mg irbesartan/12.5 mg hydrochlorothiazide tablets (3)
- 300 mg irbesartan/25 mg hydrochlorothiazide tablets (3)

4 CONTRAINDICATIONS

- Hypersensitivity to any component of this product (4)
- Anuria (4)
- Hypersensitivity to sulfonamide-derived drugs (4)

5 WARNINGS AND PRECAUTIONS

- Symptomatic hypotension with intravascular volume- or sodium-depletion. Correct volume-depletion prior to administration. Not recommended as initial therapy in volume-depleted patients (2.4, 5.2).
- Impaired hepatic function: Thiazides should be used with caution as minor fluid and electrolyte imbalances may precipitate hepatic coma (5.7).
- Impaired renal function: Use with caution. Oliguria or azotemia with acute renal failure and/or death has been reported in medications affecting the renin-angiotensin-aldosterone system (5.8).
- Thiazide diuretics may cause an exacerbation or activation of systemic lupus erythematosus (5.4).

6 ADVERSE REACTIONS

Most common adverse events (≥5% on AVALIDE and more often than on placebo) are dizziness, fatigue, and musculoskeletal pain (6.1).

To report SUSPECTED ADVERSE REACTIONS, contact Bristol-Myers Squibb at 1-800-721-5072 or FDA at 1-800-FDA-1088 or www.fda.gov/medwatch

7 DRUG INTERACTIONS

Hydrochlorothiazide (7):

- Alcohol, Barbiturates, Narcotics: Potentiation of orthostatic hypotension
- Antidiabetic Drugs: Dosage adjustment of antidiabetic may be required
- Cholestyramine and colestipol: Reduced absorption of thiazides
- Corticosteroids, ACTH: Hypokalemia, electrolyte depletion
- Lithium: Reduced renal clearance and high risk of lithium toxicity when used with diuretics. Should not be given with diuretics.
- NSAIDs: Can reduce diuretic, natriuretic, and antihypertensive effects of diuretics. Observe patient closely.

8 USE IN SPECIFIC POPULATIONS

Nursing Mothers: Potential for adverse effects in infant (8.3).

FULL PRESCRIBING INFORMATION

WARNING: USE IN PREGNANCY

When pregnancy is detected, discontinue AVALIDE as soon as possible. When used in pregnancy during the second and third trimesters, drugs that act directly on the renin-angiotensin system can cause injury and even death to the developing fetus. [See Warnings and Precautions (5.1).]

1 INDICATIONS AND USAGE

AVALIDE® (irbesartan-hydrochlorothiazide) Tablets is indicated for the treatment of hypertension.

AVALIDE may be used in patients whose blood pressure is not adequately controlled on monotherapy.

AVALIDE may also be used as initial therapy in patients who are likely to need multiple drugs to achieve their blood pressure goals.

The choice of AVALIDE as initial therapy for hypertension should be based on an assessment of potential benefits and risks.

Patients with stage 2 (moderate or severe) hypertension are at relatively high risk for cardiovascular events (such as strokes, heart attacks, and heart failure), kidney failure, and vision problems, so prompt treatment is clinically relevant. The decision to use a combination as initial therapy should be individualized and may be shaped by considerations such as the baseline blood pressure, the target goal, and the incremental likelihood of achieving goal with a combination compared with monotherapy.

Data from Studies V and VI [see Clinical Studies (14.2)] provide estimates of the probability of reaching a blood pressure goal with AVALIDE compared to irbesartan or HCTZ monotherapy. The relationship between baseline blood pressure and achievement of a SeSBP less than 140 or less than 130 mmHg or SeDBP less than 90 or less than 80 mmHg in patients treated with AVALIDE compared to patients treated with irbesartan or HCTZ monotherapy are shown in Figures 1a through 2b.

Figure 1a: Probability of Achieving SBP less than 140 mmHg in Patients from Initial Therapy Studies V (Week 8) and VI (Week 7)*

Figure 1b: Probability of Achieving SBP less than 130 mmHg in Patients from Initial Therapy Studies V (Week 8) and VI (Week 7)*

Figure 2a: Probability of Achieving DBP less than 90 mmHg in Patients from Initial Therapy Studies V (Week 8) and VI (Week 7)*

Figure 2b: Probability of Achieving DBP less than 80 mmHg in Patients from Initial Therapy Studies V (Week 8) and VI (Week 7)*

*For all probability curves, patients without blood pressure measurements at Week 7 (Study VI) and Week 8 (Study V) were counted as not reaching goal (intent-to-treat analysis).

The above graphs provide a rough approximation of the likelihood of reaching a targeted blood pressure goal (eg, Week 8 sitting systolic blood pressure less than or equal to 140 mmHg) for the treatment groups. The curve of each treatment group in each study was estimated by logistic regression modeling from all available data of that treatment group. The estimated likelihood at the right tail of each curve is less reliable due to small numbers of subjects with high baseline blood pressures.

For example, a patient with a blood pressure of 180/105 mmHg has about a 25% likelihood of achieving a goal of less than 140 mmHg (systolic) and 50% likelihood of achieving less than 90 mmHg (diastolic) on irbesartan alone (and lower still likelihoods on HCTZ alone).

The likelihood of achieving these goals on AVALIDE rises to about 40% (systolic) or 70% (diastolic).

2 DOSAGE AND ADMINISTRATION

Enter section text here

2.1 General Considerations

The side effects of irbesartan are generally rare and apparently independent of dose; those of hydrochlorothiazide are a mixture of dose-dependent (primarily hypokalemia) and dose-independent phenomena (eg, pancreatitis), the former much more common than the latter. [See Adverse Reactions (6).]

Maximum antihypertensive effects are attained within 2 to 4 weeks after a change in dose.

AVALIDE may be administered with or without food.

AVALIDE may be administered with other antihypertensive agents.

Renal impairment. The usual regimens of therapy with AVALIDE may be followed as long as the patient's creatinine clearance is greater than 30 mL/min. In patients with more severe renal impairment, loop diuretics are preferred to thiazides, so AVALIDE is not recommended.

Hepatic impairment. No dosage adjustment is necessary in patients with hepatic impairment.

2.2 Add-On Therapy

In patients not controlled on monotherapy with irbesartan or hydrochlorothiazide, the recommended doses of AVALIDE, in order of increasing mean effect, are (irbesartan-hydrochlorothiazide) 150/12.5 mg, 300/12.5 mg, and 300/25 mg. The largest incremental effect will likely be in the transition from monotherapy to 150/12.5 mg. [See Clinical Studies (14.2).]

2.3 Replacement Therapy

AVALIDE may be substituted for the titrated components.

2.4 Initial Therapy

The usual starting dose is AVALIDE 150/12.5 mg once daily. The dosage can be increased after 1 to 2 weeks of therapy to a maximum of one 300/25 mg tablet once daily as needed to control blood pressure [see Clinical Studies (14.2)]. AVALIDE is not recommended as initial therapy in patients with intravascular volume depletion [see Warnings and Precautions (5.2)].

3 DOSAGE FORMS AND STRENGTHS

AVALIDE® (irbesartan-hydrochlorothiazide) 150/12.5 mg and 300/12.5 mg tablets are peach, biconvex, and oval with a heart debossed on one side and "2775" or "2776" on the reverse side. The 300/25 mg film-coated tablet is pink, biconvex, and oval with a heart debossed on one side and "2788" on the reverse side.

4 CONTRAINDICATIONS

- AVALIDE is contraindicated in patients who are hypersensitive to any component of this product.
- Because of the hydrochlorothiazide component, this product is contraindicated in patients with anuria or hypersensitivity to other sulfonamide-derived drugs.

5 WARNINGS AND PRECAUTIONS

Enter section text here

5.1 Fetal/Neonatal Morbidity and Mortality

AVALIDE can cause fetal harm when administered to a pregnant woman. If this drug is used during pregnancy, or if the patient becomes pregnant while taking this drug, the patient should be apprised of the potential hazard to the fetus [see Use in Specific Populations (8.1)]. In several dozen published cases, angiotensin converting enzyme (ACE) inhibitor use during the second and third trimesters of pregnancy was associated with fetal and neonatal injury, including hypotension, neonatal skull hypoplasia, anuria, reversible or irreversible renal failure, and death. Similar renal findings occur in reproductive toxicology studies in rats. Thiazides cross the placenta, and use of thiazides during pregnancy is associated with a risk of fetal or neonatal jaundice, thrombocytopenia, and possibly other adverse reactions that have occurred in adults.

5.2 Hypotension in Volume- or Salt-Depleted Patients

Excessive reduction of blood pressure was rarely seen in patients with uncomplicated hypertension treated with irbesartan alone (less than 0.1%) or with irbesartan-hydrochlorothiazide (approximately 1%). Initiation of antihypertensive therapy may cause symptomatic hypotension in patients with intravascular volume- or sodium-depletion, eg, in patients treated vigorously with diuretics or in patients on dialysis. Such volume depletion should be corrected prior to administration of antihypertensive therapy.

If hypotension occurs, the patient should be placed in the supine position and, if necessary, given an intravenous infusion of normal saline. A transient hypotensive response is not a contraindication to further treatment, which usually can be continued without difficulty once the blood pressure has stabilized.

5.3 Hypersensitivity Reaction

Hydrochlorothiazide

Hypersensitivity reactions to hydrochlorothiazide may occur in patients with or without a history of allergy or bronchial asthma, but are more likely in patients with such a history.

5.4 Systemic Lupus Erythematosus

Hydrochlorothiazide

Thiazide diuretics have been reported to cause exacerbation or activation of systemic lupus erythematosus.

5.5 Lithium Interaction

Hydrochlorothiazide

Lithium generally should not be given with thiazides. [See Drug Interactions (7).]

5.6 Electrolyte and Metabolic Imbalances

Irbesartan-Hydrochlorothiazide

In double-blind clinical trials of various doses of irbesartan and hydrochlorothiazide, the incidence of hypertensive patients who developed hypokalemia (serum potassium less than 3.5 mEq/L) was 7.5% versus 6.0% for placebo; the incidence of hyperkalemia (serum potassium greater than 5.7 mEq/L) was less than 1.0% versus 1.7% for placebo. No patient discontinued due to increases or decreases in serum potassium. On average, the combination of irbesartan and hydrochlorothiazide had no effect on serum potassium. Higher doses of irbesartan ameliorated the hypokalemic response to hydrochlorothiazide.

Hydrochlorothiazide

Periodic determination of serum electrolytes to detect possible electrolyte imbalance should be performed at appropriate intervals. All patients receiving thiazide therapy should be observed for clinical signs of fluid or electrolyte imbalance: hyponatremia, hypochloremic alkalosis, and hypokalemia. Serum and urine electrolyte determinations are particularly important when the patient is vomiting excessively or receiving parenteral fluids. Warning signs or symptoms of fluid and electrolyte imbalance, irrespective of cause, include dryness of mouth, thirst, weakness, lethargy, drowsiness, restlessness, confusion, seizures, muscle pains or cramps, muscular fatigue, hypotension, oliguria, tachycardia, and gastrointestinal disturbances such as nausea and vomiting.

Hypokalemia may develop, especially with brisk diuresis, when severe cirrhosis is present, or after prolonged therapy.

Interference with adequate oral electrolyte intake will also contribute to hypokalemia. Hypokalemia may cause cardiac arrhythmia and may also sensitize or exaggerate the response of the heart to the toxic effects of digitalis (eg, increased ventricular irritability).

Although any chloride deficit is generally mild and usually does not require specific treatment except under extraordinary circumstances (as in liver disease or renal disease), chloride replacement may be required in the treatment of metabolic alkalosis.

Dilutional hyponatremia may occur in edematous patients in hot weather; appropriate therapy is water restriction, rather than administration of salt except in rare instances when the hyponatremia is life-threatening. In actual salt depletion, appropriate replacement is the therapy of choice.

Hyperuricemia may occur or frank gout may be precipitated in certain patients receiving thiazide therapy.

In diabetic patients, dosage adjustments of insulin or oral hypoglycemic agents may be required. Hyperglycemia may occur with thiazide diuretics. Thus, latent diabetes mellitus may become manifest during thiazide therapy.

The antihypertensive effects of the drug may be enhanced in the post-sympathectomy patient.

If progressive renal impairment becomes evident, consider withholding or discontinuing diuretic therapy.

Thiazides have been shown to increase the urinary excretion of magnesium; this may result in hypomagnesemia.

Thiazides may decrease urinary calcium excretion. Thiazides may cause intermittent and slight elevation of serum calcium in the absence of known disorders of calcium metabolism. Marked hypercalcemia may be evidence of hidden hyperparathyroidism. Thiazides should be discontinued before carrying out tests for parathyroid function.

Increases in cholesterol and triglyceride levels may be associated with thiazide diuretic therapy.

5.7 Hepatic Impairment

Hydrochlorothiazide

Thiazides should be used with caution in patients with impaired hepatic function or progressive liver disease, since minor alterations of fluid and electrolyte balance may precipitate hepatic coma.

5.8 Impaired Renal Function

As a consequence of inhibiting the renin-angiotensin-aldosterone system, changes in renal function may be anticipated in susceptible individuals. In patients whose renal function may depend on the activity of the renin-angiotensin-aldosterone system (eg, patients with severe congestive heart failure), treatment with ACE inhibitors has been associated with oliguria and/or progressive azotemia and (rarely) with acute renal failure and/or death. Irbesartan would be expected to behave similarly. In studies of ACE inhibitors in patients with unilateral or bilateral renal artery stenosis, increases in serum creatinine or BUN have been reported. There has been no known use of irbesartan in patients with unilateral or bilateral renal artery stenosis, but a similar effect should be anticipated.

Thiazides should be used with caution in severe renal disease. In patients with renal disease, thiazides may precipitate azotemia. Cumulative effects of the drug may develop in patients with impaired renal function.

6 ADVERSE REACTIONS

Enter section text here

6.1 Clinical Trials Experience

Because clinical trials are conducted under widely varying conditions, adverse reaction rates observed in the clinical trials of a drug cannot be directly compared to rates in the clinical trials of another drug and may not reflect the rates observed in practice. The adverse reaction information from clinical trials does, however, provide a basis for identifying the adverse events that appear to be related to drug use and for approximating rates.

Irbesartan-Hydrochlorothiazide

AVALIDE (irbesartan-hydrochlorothiazide) Tablets has been evaluated for safety in 1694 patients treated for essential hypertension in 6 clinical trials. In Studies I through IV with AVALIDE, no adverse events peculiar to this combination drug product have been observed. Adverse events have been limited to those that were reported previously with irbesartan or hydrochlorothiazide (HCTZ). The overall incidence of adverse events was similar with the combination and placebo. In general, treatment with AVALIDE was well tolerated. For the most part, adverse events have been mild and transient in nature and have not required discontinuation of therapy. In controlled clinical trials, discontinuation of AVALIDE therapy due to clinical adverse events was required in only 3.6%. This incidence was significantly less (p=0.023) than the 6.8% of patients treated with placebo who discontinued therapy.

In these double-blind controlled clinical trials, the following adverse events reported with AVALIDE occurred in ≥1% of patients, and more often on the irbesartan-hydrochlorothiazide combination than on placebo, regardless of drug relationship:

 | Irbesartan/HCTZ (n=898) (%) | Placebo (n=236) (%) | Irbesartan (n=400) (%) | HCTZ (n=380) (%)
Body as a Whole
Chest Pain | 2 | 1 | 2 | 2
Fatigue | 7 | 3 | 4 | 3
Influenza | 3 | 1 | 2 | 2
Cardiovascular
Edema | 3 | 3 | 2 | 2
Tachycardia | 1 | 0 | 1 | 1
Gastrointestinal
Abdominal Pain | 2 | 1 | 2 | 2
Dyspepsia/heartburn | 2 | 1 | 0 | 2
Nausea/vomiting | 3 | 0 | 2 | 0
Immunology
Allergy | 1 | 0 | 1 | 1
Musculoskeletal
Musculoskeletal Pain | 7 | 5 | 6 | 10
Nervous System
Dizziness | 8 | 4 | 6 | 5
Dizziness Orthostatic | 1 | 0 | 1 | 1
Renal/Genitourinary
Abnormality Urination | 2 | 1 | 1 | ct2

The following adverse events were also reported at a rate of 1% or greater, but were as, or more, common in the placebo group: headache, sinus abnormality, cough, URI, pharyngitis, diarrhea, rhinitis, urinary tract infection, rash, anxiety/nervousness, and muscle cramp.

Adverse events occurred at about the same rates in men and women, older and younger patients, and black and non-black patients.

Adverse events in Studies V and VI were similar to those described above in Studies I through IV.

Irbesartan

Other adverse events that have been reported with irbesartan, without regard to causality, are listed below:

Body as a Whole: fever, chills, orthostatic effects, facial edema, upper extremity edema

Cardiovascular: flushing, hypertension, cardiac murmur, myocardial infarction, angina pectoris, hypotension, syncope, arrhythmic/conduction disorder, cardiorespiratory arrest, heart failure, hypertensive crisis

Dermatologic: pruritus, dermatitis, ecchymosis, erythema face, urticaria

Endocrine/Metabolic/Electrolyte Imbalances: sexual dysfunction, libido change, gout

Gastrointestinal: diarrhea, constipation, gastroenteritis, flatulence, abdominal distention

Musculoskeletal/Connective Tissue: musculoskeletal trauma, extremity swelling, muscle cramp, arthritis, muscle ache, musculoskeletal chest pain, joint stiffness, bursitis, muscle weakness

Nervous System: anxiety/nervousness, sleep disturbance, numbness, somnolence, vertigo, emotional disturbance, depression, paresthesia, tremor, transient ischemic attack, cerebrovascular accident

Renal/Genitourinary: prostate disorder

Respiratory: cough, upper respiratory infection, epistaxis, tracheobronchitis, congestion, pulmonary congestion, dyspnea, wheezing

Special Senses: vision disturbance, hearing abnormality, ear infection, ear pain, conjunctivitis

Hydrochlorothiazide

Other adverse events that have been reported with hydrochlorothiazide, without regard to causality, are listed below:

Body as a Whole: weakness

Digestive: pancreatitis, jaundice (intrahepatic cholestatic jaundice), sialadenitis, cramping, gastric irritation

Hematologic: aplastic anemia, agranulocytosis, leukopenia, hemolytic anemia, thrombocytopenia

Hypersensitivity: purpura, photosensitivity, urticaria, necrotizing angiitis (vasculitis and cutaneous vasculitis), fever, respiratory distress including pneumonitis and pulmonary edema, anaphylactic reactions

Metabolic: hyperglycemia, glycosuria, hyperuricemia

Musculoskeletal: muscle spasm

Nervous System/Psychiatric: restlessness

Renal: renal failure, renal dysfunction, interstitial nephritis

Skin: erythema multiforme including Stevens-Johnson syndrome, exfoliative dermatitis including toxic epidermal necrolysis

Special Senses: transient blurred vision, xanthopsia

Initial Therapy

In the moderate hypertension Study V (mean SeDBP between 90 and 110 mmHg), the types and incidences of adverse events reported for patients treated with AVALIDE were similar to the adverse event profile in patients on initial irbesartan or HCTZ monotherapy. There were no reported events of syncope in the AVALIDE treatment group and there was one reported event in the HCTZ treatment group. The incidences of pre-specified adverse events on AVALIDE, irbesartan, and HCTZ, respectively, were: 0.9%, 0%, and 0% for hypotension; 3.0%, 3.8%, and 1.0% for dizziness; 5.5%, 3.8%, and 4.8% for headache; 1.2%, 0%, and 1.0% for hyperkalemia; and 0.9%, 0%, and 0% for hypokalemia. The rates of discontinuation due to adverse events on AVALIDE, irbesartan alone, and HCTZ alone were 6.7%, 3.8%, and 4.8%.

In the severe hypertension (SeDBP ≥110 mmHg) Study VI, the overall pattern of adverse events reported through 7 weeks of follow-up was similar in patients treated with AVALIDE as initial therapy and in patients treated with irbesartan as initial therapy. The incidences of the pre-specified adverse events on AVALIDE and irbesartan, respectively, were: 0% and 0% for syncope; 0.6% and 0% for hypotension; 3.6% and 4.0% for dizziness; 4.3% and 6.6% for headache; 0.2% and 0% for hyperkalemia; and 0.6% and 0.4% for hypokalemia. The rates of discontinuation due to adverse events were 2.1% and 2.2%. [See Clinical Studies (14.2).]

6.2 Post-Marketing Experience

The following adverse reactions have been identified during post-approval use of AVALIDE. Because these reactions are reported voluntarily from a population of uncertain size, it is not always possible to reliably estimate their frequency or establish a causal relationship to drug exposure. Decisions to include these reactions in labeling are typically based on one or more of the following factors: (1) seriousness of the reaction, (2) frequency of reporting, or (3) strength of causal connection to AVALIDE.

The following have been very rarely reported: urticaria; angioedema (involving swelling of the face, lips, pharynx, and/or tongue); and hepatitis. Hyperkalemia has been rarely reported.

Very rare cases of jaundice have been reported with irbesartan.

Rare cases of rhabdomyolysis have been reported in patients receiving angiotensin II receptor blockers.

6.3 Laboratory Abnormalities

In controlled clinical trials, clinically important changes in standard laboratory parameters were rarely associated with administration of AVALIDE.

Creatinine, Blood Urea Nitrogen: Minor increases in blood urea nitrogen (BUN) or serum creatinine were observed in 2.3% and 1.1%, respectively, of patients with essential hypertension treated with AVALIDE alone. No patient discontinued taking AVALIDE due to increased BUN. One patient discontinued taking AVALIDE due to a minor increase in serum creatinine.

Liver Function Tests: Occasional elevations of liver enzymes and/or serum bilirubin have occurred. In patients with essential hypertension treated with AVALIDE alone, one patient was discontinued due to elevated liver enzymes.

Serum Electrolytes: [See Warnings and Precautions (5.2, 5.6).]

7 DRUG INTERACTIONS

Irbesartan

No significant drug-drug interactions have been reported with irbesartan. [See Clinical Pharmacology (12.3).]

Hydrochlorothiazide

When administered concurrently the following drugs may interact with thiazide diuretics:

Alcohol, Barbiturates, or Narcotics: potentiation of orthostatic hypotension may occur.

Antidiabetic Drugs (oral agents and insulin): dosage adjustment of the antidiabetic drug may be required.

Other Antihypertensive Drugs: additive effect or potentiation.

Cholestyramine and Colestipol Resins: absorption of hydrochlorothiazide is impaired in the presence of anionic exchange resins. Single doses of either cholestyramine or colestipol resins bind the hydrochlorothiazide and reduce its absorption from the gastrointestinal tract by up to 85% and 43%, respectively.

Corticosteroids, ACTH: intensified electrolyte depletion, particularly hypokalemia.

Pressor Amines (eg, Norepinephrine): possible decreased response to pressor amines but not sufficient to preclude their use.

Skeletal Muscle Relaxants, Nondepolarizing (eg, Tubocurarine): possible increased responsiveness to the muscle relaxant.

Lithium: should not generally be given with diuretics. Diuretic agents reduce the renal clearance of lithium and add a high risk of lithium toxicity. Refer to the package insert for lithium preparations before use of such preparations with AVALIDE. [See Warnings and Precautions (5.5).]

Non-steroidal Anti-inflammatory Drugs: in some patients, the administration of a non-steroidal anti-inflammatory agent can reduce the diuretic, natriuretic, and antihypertensive effects of loop, potassium-sparing and thiazide diuretics. Therefore, when AVALIDE (irbesartan-hydrochlorothiazide) Tablets and non-steroidal anti-inflammatory agents are used concomitantly, the patient should be observed closely to determine if the desired effect of the diuretic is obtained.

8 USE IN SPECIFIC POPULATIONS

Enter section text here

8.1 Pregnancy

Pregnancy Category D

See Warnings and Precautions (5.1).

AVALIDE contains both irbesartan (an angiotensin II receptor antagonist) and hydrochlorothiazide (a thiazide diuretic). When administered during the second or third trimester of pregnancy, drugs that act directly on the renin-angiotensin system (RAS) can cause fetal and neonatal morbidity and death. Thiazides cross the placenta, and use of thiazides during pregnancy is associated with a risk of fetal or neonatal jaundice, thrombocytopenia, and possibly other adverse reactions that have occurred in adults. AVALIDE can cause fetal harm when administered to a pregnant woman. If this drug is used during pregnancy, or if the patient becomes pregnant while taking this drug, the patient should be apprised of the potential hazard to the fetus.

Angiotensin II receptor antagonists, like irbesartan, and ACE inhibitors exert similar effects on the RAS. In several dozen published cases, ACE inhibitor use during the second and third trimesters of pregnancy was associated with fetal and neonatal injury, including hypotension, neonatal skull hypoplasia, anuria, reversible or irreversible renal failure, and death. Oligohydramnios was also reported, presumably from decreased fetal renal function. In this setting, oligohydramnios was associated with fetal limb contractures, craniofacial deformation, and hypoplastic lung development. Prematurity, intrauterine growth retardation, and patent ductus arteriosus were also reported, although it is not clear whether these occurrences were due to exposure to the drug. These adverse effects do not appear to have resulted from intrauterine drug exposure that has been limited to the first trimester.

When pregnancy occurs in a patient using AVALIDE, the physician should discontinue AVALIDE treatment as soon as possible. The physician should inform the patient about potential risks to the fetus based on the time of gestational exposure to AVALIDE (first trimester only or later). If exposure occurs beyond the first trimester, an ultrasound examination should be done.

In rare cases when another antihypertensive agent cannot be used to treat the pregnant patient, serial ultrasound examinations should be performed to assess the intraamniotic environment. Routine fetal testing with non-stress tests, biophysical profiles, and/or contraction stress tests may be appropriate based on gestational age and standards of care in the community. If oligohydramnios occurs in these situations, individualized decisions about continuing or discontinuing AVALIDE treatment and about pregnancy management should be made by the patient, her physician, and experts in the management of high risk pregnancy. Patients and physicians should be aware that oligohydramnios may not appear until after the fetus has sustained irreversible injury.

Infants with histories of in utero exposure to AVALIDE should be closely observed for hypotension, oliguria, and hyperkalemia. If oliguria occurs, these infants may require blood pressure and renal perfusion support. Exchange transfusion or dialysis may be required to reverse hypotension and/or support decreased renal function.

Irbesartan crosses the placenta in rats and rabbits. In pregnant rats given irbesartan at doses greater than the maximum recommended human dose (MRHD), fetuses showed increased incidences of renal pelvic cavitation, hydroureter and/or absence of renal papilla. Subcutaneous edema also occurred in fetuses at doses about 4 times the MRHD (based on body surface area). These anomalies occurred when pregnant rats received irbesartan through Day 20 of gestation but not when drug was stopped on gestation Day 15. The observed effects are believed to be late gestational effects of the drug. Pregnant rabbits given oral doses of irbesartan equivalent to 1.5 times the MRHD experienced a high rate of maternal mortality and abortion. Surviving females had a slight increase in early resorptions and a corresponding decrease in live fetuses [see Nonclinical Toxicology (13.2)].

Radioactivity was present in the rat and rabbit fetus during late gestation and in rat milk following oral doses of radiolabeled irbesartan.

When pregnant mice and rats were given hydrochlorothiazide at doses up to 3000 and 1000 mg/kg/day, respectively (about 600 and 400 times the MRHD) during their respective periods of major organogenesis, there was no evidence of fetal harm.

A development toxicity study was performed in rats with doses of 50/50 mg/kg/day and 150/150 mg/kg/day irbesartan-hydrochlorothiazide. Although the high dose combination appeared to be more toxic to the dams than either drug alone, there did not appear to be an increase in toxicity to the developing embryos.

8.3 Nursing Mothers

It is not known whether irbesartan is excreted in human milk, but irbesartan or some metabolite of irbesartan is secreted at low concentration in the milk of lactating rats.

Thiazides appear in human milk. Because of the potential for adverse effects on the nursing infant, a decision should be made whether to discontinue nursing or discontinue the drug, taking into account the importance of the drug to the mother.

8.4 Pediatric Use

Safety and effectiveness in pediatric patients have not been established.

8.5 Geriatric Use

Of 1694 patients receiving AVALIDE in controlled clinical studies of hypertension, 264 (15.6%) were 65 years and over, while 45 (2.7%) were 75 years and over. No overall differences in safety or effectiveness were observed between these patients and younger patients, but greater sensitivity of some older individuals cannot be ruled out. [See Clinical Pharmacology (12.3) and Clinical Studies (14).]

10 OVERDOSAGE

Irbesartan

No data are available in regard to overdosage in humans. However, daily doses of 900 mg for 8 weeks were well tolerated. The most likely manifestations of overdosage are expected to be hypotension and tachycardia; bradycardia might also occur from overdose. Irbesartan is not removed by hemodialysis.

To obtain up-to-date information about the treatment of overdosage, a good resource is a certified regional Poison Control Center. Telephone numbers of certified Poison Control Centers are listed in the Physicians’ Desk Reference (PDR). In managing overdose, consider the possibilities of multiple-drug interactions, drug-drug interactions, and unusual drug kinetics in the patient.

Laboratory determinations of serum levels of irbesartan are not widely available, and such determinations have, in any event, no established role in the management of irbesartan overdose.

Acute oral toxicity studies with irbesartan in mice and rats indicated acute lethal doses were in excess of 2000 mg/kg, about 25- and 50-fold the MRHD (300 mg) on a mg/m^2 basis, respectively.

Hydrochlorothiazide

The most common signs and symptoms of overdose observed in humans are those caused by electrolyte depletion (hypokalemia, hypochloremia, hyponatremia) and dehydration resulting from excessive diuresis. If digitalis has also been administered, hypokalemia may accentuate cardiac arrhythmias. The degree to which hydrochlorothiazide is removed by hemodialysis has not been established. The oral LD50 of hydrochlorothiazide is greater than 10 g/kg in both mice and rats.

11 DESCRIPTION

AVALIDE (irbesartan-hydrochlorothiazide) Tablets is a combination of an angiotensin II receptor antagonist (AT1 subtype), irbesartan, and a thiazide diuretic, hydrochlorothiazide (HCTZ).

Irbesartan is a non-peptide compound, chemically described as a 2-butyl-3-[p-(o-1H-tetrazol-5-ylphenyl)benzyl]-1,3-diazaspiro[4.4]non-1-en-4-one. Its empirical formula is C25H28N6O, and its structural formula is:

Irbesartan is a white to off-white crystalline powder with a molecular weight of 428.5. It is a nonpolar compound with a partition coefficient (octanol/water) of 10.1 at pH of 7.4. Irbesartan is slightly soluble in alcohol and methylene chloride and practically insoluble in water.

Hydrochlorothiazide is 6-chloro-3,4-dihydro-2H-1,2,4-benzothiadiazine-7-sulfonamide 1,1-dioxide. Its empirical formula is C7H8ClN3O4S2 and its structural formula is:

Hydrochlorothiazide is a white, or practically white, crystalline powder with a molecular weight of 297.7. Hydrochlorothiazide is slightly soluble in water and freely soluble in sodium hydroxide solution.

AVALIDE is available for oral administration in tablets containing either 150 mg or 300 mg of irbesartan combined with 12.5 mg of hydrochlorothiazide or 300 mg of irbesartan combined with 25 mg hydrochlorothiazide. Inactive ingredients include: lactose monohydrate, microcrystalline cellulose, pregelatinized starch, croscarmellose sodium, ferric oxide red, ferric oxide yellow, silicon dioxide, and magnesium stearate. In addition, the 300/25 mg pink film-coated tablet contains ferric oxide black, hypromellose-2910, PEG-3350, titanium dioxide, and carnauba wax.

12 CLINICAL PHARMACOLOGY

Enter section text here

12.1 Mechanism of Action

Irbesartan

Angiotensin II is a potent vasoconstrictor formed from angiotensin I in a reaction catalyzed by angiotensin-converting enzyme (ACE, kininase II). Angiotensin II is the principal pressor agent of the RAS and also stimulates aldosterone synthesis and secretion by adrenal cortex, cardiac contraction, renal resorption of sodium, activity of the sympathetic nervous system, and smooth muscle cell growth. Irbesartan blocks the vasoconstrictor and aldosterone-secreting effects of angiotensin II by selectively binding to the AT1 angiotensin II receptor. There is also an AT2 receptor in many tissues, but it is not involved in cardiovascular homeostasis.

Irbesartan is a specific competitive antagonist of AT1 receptors with a much greater affinity (more than 8500-fold) for the AT1 receptor than for the AT2 receptor, and no agonist activity.

Blockade of the AT1 receptor removes the negative feedback of angiotensin II on renin secretion, but the resulting increased plasma renin activity and circulating angiotensin II do not overcome the effects of irbesartan on blood pressure.

Irbesartan does not inhibit ACE or renin or affect other hormone receptors or ion channels known to be involved in the cardiovascular regulation of blood pressure and sodium homeostasis. Because irbesartan does not inhibit ACE, it does not affect the response to bradykinin; whether this has clinical relevance is not known.

Hydrochlorothiazide

Hydrochlorothiazide is a thiazide diuretic. Thiazides affect the renal tubular mechanisms of electrolyte reabsorption, directly increasing excretion of sodium and chloride in approximately equivalent amounts. Indirectly, the diuretic action of hydrochlorothiazide reduces plasma volume, with consequent increases in plasma renin activity, increases in aldosterone secretion, increases in urinary potassium loss, and decreases in serum potassium. The renin-aldosterone link is mediated by angiotensin II, so coadministration of an angiotensin II receptor antagonist tends to reverse the potassium loss associated with these diuretics.

The mechanism of the antihypertensive effect of thiazides is not fully understood.

12.2 Pharmacodynamics

Irbesartan

In healthy subjects, single oral irbesartan doses of up to 300 mg produced dose-dependent inhibition of the pressor effect of angiotensin II infusions. Inhibition was complete (100%) 4 hours following oral doses of 150 mg or 300 mg and partial inhibition was sustained for 24 hours (60% and 40% at 300 mg and 150 mg, respectively).

In hypertensive patients, angiotensin II receptor inhibition following chronic administration of irbesartan causes a 1.5- to 2-fold rise in angiotensin II plasma concentration and a 2- to 3-fold increase in plasma renin levels. Aldosterone plasma concentrations generally decline following irbesartan administration, but serum potassium levels are not significantly affected at recommended doses.

In hypertensive patients, chronic oral doses of irbesartan (up to 300 mg) had no effect on glomerular filtration rate, renal plasma flow or filtration fraction. In multiple dose studies in hypertensive patients, there were no clinically important effects on fasting triglycerides, total cholesterol, HDL-cholesterol, or fasting glucose concentrations. There was no effect on serum uric acid during chronic oral administration and no uricosuric effect.

Hydrochlorothiazide

After oral administration of hydrochlorothiazide, diuresis begins within 2 hours, peaks in about 4 hours and lasts about 6 to 12 hours.

12.3 Pharmacokinetics

Irbesartan

Irbesartan is an orally active agent that does not require biotransformation into an active form. The oral absorption of irbesartan is rapid and complete with an average absolute bioavailability of 60% to 80%. Following oral administration of irbesartan, peak plasma concentrations of irbesartan are attained at 1.5 to 2 hours after dosing. Food does not affect the bioavailability of irbesartan.

Irbesartan exhibits linear pharmacokinetics over the therapeutic dose range.

The terminal elimination half-life of irbesartan averaged 11 to 15 hours. Steady-state concentrations are achieved within 3 days. Limited accumulation of irbesartan (less than 20%) is observed in plasma upon repeated once-daily dosing.

Hydrochlorothiazide

When plasma levels have been followed for at least 24 hours, the plasma half-life has been observed to vary between 5.6 and 14.8 hours.

Metabolism and Elimination

Irbesartan

Irbesartan is metabolized via glucuronide conjugation and oxidation. Following oral or intravenous administration of ^14C-labeled irbesartan, more than 80% of the circulating plasma radioactivity is attributable to unchanged irbesartan. The primary circulating metabolite is the inactive irbesartan glucuronide conjugate (approximately 6%). The remaining oxidative metabolites do not add appreciably to irbesartan’s pharmacologic activity.

Irbesartan and its metabolites are excreted by both biliary and renal routes. Following either oral or intravenous administration of ^14C-labeled irbesartan, about 20% of radioactivity is recovered in the urine and the remainder in the feces, as irbesartan or irbesartan glucuronide.

In vitro studies of irbesartan oxidation by cytochrome P450 isoenzymes indicated irbesartan was oxidized primarily by 2C9; metabolism by 3A4 was negligible. Irbesartan was neither metabolized by, nor did it substantially induce or inhibit, isoenzymes commonly associated with drug metabolism (1A1, 1A2, 2A6, 2B6, 2D6, 2E1). There was no induction or inhibition of 3A4.

Hydrochlorothiazide

Hydrochlorothiazide is not metabolized but is eliminated rapidly by the kidney. At least 61% of the oral dose is eliminated unchanged within 24 hours.

Distribution

Irbesartan

Irbesartan is 90% bound to serum proteins (primarily albumin and α1-acid glycoprotein) with negligible binding to cellular components of blood. The average volume of distribution is 53 to 93 liters. Total plasma and renal clearances are in the range of 157 to 176 mL/min and 3.0 to 3.5 mL/min, respectively. With repetitive dosing, irbesartan accumulates to no clinically relevant extent.

Studies in animals indicate that radiolabeled irbesartan weakly crosses the blood-brain barrier and placenta. Irbesartan is excreted in the milk of lactating rats.

Hydrochlorothiazide

Hydrochlorothiazide crosses the placental but not the blood-brain barrier and is excreted in breast milk.

Pediatric

Irbesartan-hydrochlorothiazide pharmacokinetics have not been investigated in patients less than 18 years of age.

Gender

No gender-related differences in pharmacokinetics were observed in healthy elderly (age 65 to 80 years) or in healthy young (age 18 to 40 years) subjects. In studies of hypertensive patients, there was no gender difference in half-life or accumulation, but somewhat higher plasma concentrations of irbesartan were observed in females (11% to 44%). No gender-related dosage adjustment is necessary.

Geriatric

In elderly subjects (age 65 to 80 years), irbesartan elimination half-life was not significantly altered, but AUC and Cmax values were about 20% to 50% greater than those of young subjects (age 18 to 40 years). No dosage adjustment is necessary in the elderly.

Race

In healthy black subjects, irbesartan AUC values were approximately 25% greater than whites; there were no differences in Cmax values.

Renal Insufficiency

The pharmacokinetics of irbesartan were not altered in patients with renal impairment or in patients on hemodialysis. Irbesartan is not removed by hemodialysis. No dosage adjustment is necessary in patients with mild to severe renal impairment unless a patient with renal impairment is also volume depleted. [See Warnings and Precautions (5.2).]

Hepatic Insufficiency

The pharmacokinetics of irbesartan following repeated oral administration were not significantly affected in patients with mild to moderate cirrhosis of the liver. No dosage adjustment is necessary in patients with hepatic insufficiency.

Drug-Drug Interactions

No significant drug-drug pharmacokinetic (or pharmacodynamic) interactions have been found in interaction studies with hydrochlorothiazide, digoxin, warfarin, and nifedipine.

In vitro studies show significant inhibition of the formation of oxidized irbesartan metabolites with the known cytochrome CYP 2C9 substrates/inhibitors sulphenazole, tolbutamide and nifedipine. However, in clinical studies the consequences of concomitant irbesartan on the pharmacodynamics of warfarin were negligible. Concomitant nifedipine or hydrochlorothiazide had no effect on irbesartan pharmacokinetics. Based on in vitro data, no interaction would be expected with drugs whose metabolism is dependent upon cytochrome P450 isoenzymes 1A1, 1A2, 2A6, 2B6, 2D6, 2E1, or 3A4.

In separate studies of patients receiving maintenance doses of warfarin, hydrochlorothiazide, or digoxin, irbesartan administration for 7 days had no effect on the pharmacodynamics of warfarin (prothrombin time) or the pharmacokinetics of digoxin. The pharmacokinetics of irbesartan were not affected by coadministration of nifedipine or hydrochlorothiazide.

13 NONCLINICAL TOXICOLOGY

Enter section text here

13.1 Carcinogenesis, Mutagenesis, Impairment of Fertility

Irbesartan-Hydrochlorothiazide

No carcinogenicity studies have been conducted with the irbesartan-hydrochlorothiazide combination.

Irbesartan-hydrochlorothiazide was not mutagenic in standard in vitro tests (Ames microbial test and Chinese hamster mammalian-cell forward gene-mutation assay). Irbesartan-hydrochlorothiazide was negative in tests for induction of chromosomal aberrations (in vitro—human lymphocyte assay; in vivo—mouse micronucleus study).

The combination of irbesartan and hydrochlorothiazide has not been evaluated in definitive studies of fertility.

Irbesartan

No evidence of carcinogenicity was observed when irbesartan was administered at doses of up to 500/1000 mg/kg/day (males/females, respectively) in rats and 1000 mg/kg/day in mice for up to 2 years. For male and female rats, 500 mg/kg/day provided an average systemic exposure to irbesartan (AUC0-24 hours, bound plus unbound) about 3 and 11 times, respectively, the average systemic exposure in humans receiving the maximum recommended dose (MRD) of 300 mg irbesartan/day, whereas 1000 mg/kg/day (administered to females only) provided an average systemic exposure about 21 times that reported for humans at the MRD. For male and female mice, 1000 mg/kg/day provided an exposure to irbesartan about 3 and 5 times, respectively, the human exposure at 300 mg/day.

Irbesartan was not mutagenic in a battery of in vitro tests (Ames microbial test, rat hepatocyte DNA repair test, V79 mammalian-cell forward gene-mutation assay). Irbesartan was negative in several tests for induction of chromosomal aberrations (in vitro—human lymphocyte assay; in vivo—mouse micronucleus study).

Irbesartan had no adverse effects on fertility or mating of male or female rats at oral doses ≤650 mg/kg/day, the highest dose providing a systemic exposure to irbesartan (AUC0-24 hours, bound plus unbound) about 5 times that found in humans receiving the MRD of 300 mg/day.

Hydrochlorothiazide

Two-year feeding studies in mice and rats conducted under the auspices of the National Toxicology Program (NTP) uncovered no evidence of a carcinogenic potential of hydrochlorothiazide in female mice (at doses of up to approximately 600 mg/kg/day) or in male and female rats (at doses of up to approximately 100 mg/kg/day). The NTP, however, found equivocal evidence for hepatocarcinogenicity in male mice.

Hydrochlorothiazide was not genotoxic in vitro in the Ames mutagenicity assay of Salmonella typhimurium strains TA 98, TA 100, TA 1535, TA 1537, and TA 1538 and in the Chinese Hamster Ovary (CHO) test for chromosomal aberrations, or in vivo in assays using mouse germinal cell chromosomes, Chinese hamster bone marrow chromosomes, and the Drosophila sex-linked recessive lethal trait gene. Positive test results were obtained only in the in vitro CHO Sister Chromatid Exchange (clastogenicity) and in the Mouse Lymphoma Cell (mutagenicity) assays, using concentrations of hydrochlorothiazide from 43 to 1300 μg/mL, and in the Aspergillus nidulans non-disjunction assay at an unspecified concentration.

Hydrochlorothiazide had no adverse effects on the fertility of mice and rats of either sex in studies wherein these species were exposed, via their diet, to doses of up to 100 and 4 mg/kg, respectively, prior to mating and throughout gestation.

13.2 Animal Toxicology and/or Pharmacology

Reproductive Toxicology Studies

When pregnant rats were treated with irbesartan from day 0 to day 20 of gestation (oral doses of 50, 180, and 650 mg/kg/day), increased incidences of renal pelvic cavitation, hydroureter and/or absence of renal papilla were observed in fetuses at doses ≥50 mg/kg/day (approximately equivalent to the MRHD, 300 mg/day, on a body surface area basis). Subcutaneous edema was observed in fetuses at doses ≥180 mg/kg/day (about 4 times the MRHD on a body surface area basis). As these anomalies were not observed in rats in which irbesartan exposure (oral doses of 50, 150, and 450 mg/kg/day) was limited to gestation days 6 to 15, they appear to reflect late gestational effects of the drug. In pregnant rabbits, oral doses of 30 mg irbesartan/kg/day were associated with maternal mortality and abortion. Surviving females receiving this dose (about 1.5 times the MRHD on a body surface area basis) had a slight increase in early resorptions and a corresponding decrease in live fetuses. Irbesartan was found to cross the placental barrier in rats and rabbits.

14 CLINICAL STUDIES

Enter section text here

14.1 Irbesartan Monotherapy

The antihypertensive effects of irbesartan were examined in 7 major placebo-controlled, 8- to 12-week trials in patients with baseline diastolic blood pressures of 95 to 110 mmHg. Doses of 1 to 900 mg were included in these trials in order to fully explore the dose-range of irbesartan. These studies allowed a comparison of once- or twice-daily regimens at 150 mg/day, comparisons of peak and trough effects, and comparisons of response by gender, age, and race. Two of the 7 placebo-controlled trials identified above and 2 additional placebo-controlled studies examined the antihypertensive effects of irbesartan and hydrochlorothiazide in combination.

The 7 studies of irbesartan monotherapy included a total of 1915 patients randomized to irbesartan (1 to 900 mg) and 611 patients randomized to placebo. Once-daily doses of 150 to 300 mg provided statistically and clinically significant decreases in systolic and diastolic blood pressure with trough (24-hour post-dose) effects after 6 to 12 weeks of treatment compared to placebo, of about 8 to 10/5 to 6 mmHg and 8 to 12/5 to 8 mmHg, respectively. No further increase in effect was seen at dosages greater than 300 mg. The dose-response relationships for effects on systolic and diastolic pressure are shown in Figures 3 and 4.

Once-daily administration of therapeutic doses of irbesartan gave peak effects at around 3 to 6 hours and, in one continuous ambulatory blood pressure monitoring study, again around 14 hours. This was seen with both once-daily and twice-daily dosing. Trough-to-peak ratios for systolic and diastolic response were generally between 60% to 70%. In a continuous ambulatory blood pressure monitoring study, once-daily dosing with 150 mg gave trough and mean 24-hour responses similar to those observed in patients receiving twice-daily dosing at the same total daily dose.

Analysis of age, gender, and race subgroups of patients showed that men and women, and patients over and under 65 years of age, had generally similar responses. Irbesartan was effective in reducing blood pressure regardless of race, although the effect was somewhat less in blacks (usually a low-renin population). Black patients typically show an improved response with the addition of a low dose diuretic (eg, 12.5 mg hydrochlorothiazide).

The effect of irbesartan is apparent after the first dose and is close to the full observed effect at 2 weeks. At the end of the 8-week exposure, about 2/3 of the antihypertensive effect was still present 1 week after the last dose. Rebound hypertension was not observed. There was essentially no change in average heart rate in irbesartan-treated patients in controlled trials.

14.2 Irbesartan-Hydrochlorothiazide

The antihypertensive effects of AVALIDE (irbesartan-hydrochlorothiazide) Tablets were examined in 4 placebo-controlled studies in patients with mild-moderate hypertension (mean seated diastolic blood pressure [SeDBP] between 90 and 110 mmHg), one study in patients with moderate hypertension (mean seated systolic blood pressure [SeSBP] 160 to 179 mmHg or SeDBP 100 to 109 mmHg), and one study in patients with severe hypertension (mean SeDBP ≥110 mmHg) of 8 to 12 weeks. These trials included 3149 patients randomized to fixed doses of irbesartan (37.5 to 300 mg) and concomitant hydrochlorothiazide (6.25 to 25 mg).

Study I was a factorial study that compared all combinations of irbesartan (37.5 mg, 100 mg, and 300 mg or placebo) and hydrochlorothiazide (6.25 mg, 12.5 mg, and 25 mg or placebo).

Study II compared the irbesartan-hydrochlorothiazide combinations of 75/12.5 mg and 150/12.5 mg to their individual components and placebo.

Study III investigated the ambulatory blood pressure responses to irbesartan-hydrochlorothiazide (75/12.5 mg and 150/12.5 mg) and placebo after 8 weeks of dosing.

Study IV investigated the effects of the addition of irbesartan (75 or 150 mg) in patients not controlled (SeDBP 93-120 mmHg) on hydrochlorothiazide (25 mg) alone. In Studies I–III, the addition of irbesartan 150 to 300 mg to hydrochlorothiazide doses of 6.25, 12.5, or 25 mg produced further dose-related reductions in blood pressure at trough of 8 to 10 mmHg/3 to 6 mmHg, similar to those achieved with the same monotherapy dose of irbesartan. The addition of hydrochlorothiazide to irbesartan produced further dose-related reductions in blood pressure at trough (24 hours post-dose) of 5 to 6/2 to 3 mmHg (12.5 mg) and 7 to 11/4 to 5 mmHg (25 mg), also similar to effects achieved with hydrochlorothiazide alone. Once-daily dosing with 150 mg irbesartan and 12.5 mg hydrochlorothiazide, 300 mg irbesartan and 12.5 mg hydrochlorothiazide, or 300 mg irbesartan and 25 mg hydrochlorothiazide produced mean placebo-adjusted blood pressure reductions at trough (24 hours post-dosing) of about 13 to 15/7 to 9 mmHg, 14/9 to 12 mmHg, and 19 to 21/11 to 12 mmHg, respectively. Peak effects occurred at 3 to 6 hours, with the trough-to-peak ratios greater than 65%.

In Study IV, the addition of irbesartan (75–150 mg) gave an additive effect (systolic/diastolic) at trough (24 hours post-dosing) of 11/7 mmHg.

Initial Therapy

Studies V and VI had no placebo group, so effects described below are not all attributable to irbesartan or HCTZ.

Study V was conducted in patients with a mean baseline blood pressure of 162/98 mmHg and compared the change from baseline in SeSBP at 8 weeks between the combination group (irbesartan and HCTZ 150/12.5 mg), to irbesartan (150 mg) and to HCTZ (12.5 mg). These initial study regimens were increased at 2 weeks to AVALIDE 300/25 mg, irbesartan 300 mg, or to HCTZ 25 mg, respectively.

Mean reductions from baseline for SeDBP and SeSBP at trough were 14.6 mmHg and 27.1 mmHg for patients treated with AVALIDE, 11.6 mmHg and 22.1 mmHg for patients treated with irbesartan, and 7.3 mmHg and 15.7 mmHg for patients treated with HCTZ at 8 weeks, respectively. For patients treated with AVALIDE, the mean change from baseline in SeDBP was 3.0 mmHg lower (p=0.0013) and the mean change from baseline in SeSBP was 5.0 mmHg lower (p=0.0016) compared to patients treated with irbesartan, and 7.4 mmHg lower (p less than 0.0001) and 11.3 mmHg lower (p less than 0.0001) compared to patients treated with HCTZ, respectively. Withdrawal rates were 3.8% on irbesartan, 4.8% on HCTZ, and 6.7% on AVALIDE.

Study VI was conducted in patients with a mean baseline blood pressure of 172/113 mmHg and compared trough SeDBP at 5 weeks between the combination group (irbesartan and HCTZ 150/12.5 mg) and irbesartan (150 mg). These initial study regimens were increased at 1 week to AVALIDE 300/25 mg or to irbesartan 300 mg, respectively.

At 5 weeks, mean reductions from baseline for SeDBP and SeSBP at trough were 24.0 mmHg and 30.8 mmHg for patients treated with AVALIDE and 19.3 mmHg and 21.1 mmHg for patients treated with irbesartan, respectively. The mean SeDBP was 4.7 mmHg lower (p less than 0.0001) and the mean SeSBP was 9.7 mmHg lower (p less than 0.0001) in the group treated with AVALIDE than in the group treated with irbesartan. Patients treated with AVALIDE achieved more rapid blood pressure control with significantly lower SeDBP and SeSBP and greater blood pressure control at every assessment (Week 1, Week 3, Week 5, and Week 7). Maximum effects were seen at Week 7.

Withdrawal rates were 2.2% on irbesartan and 2.1% on AVALIDE.

In Studies I–VI, there was no difference in response for men and women or in patients over or under 65 years of age. Black patients had a larger response to hydrochlorothiazide than non-black patients and a smaller response to irbesartan. The overall response to the combination was similar for black and non-black patients.

16 HOW SUPPLIED/STORAGE AND HANDLING

Enter section text here

16.1 How Supplied

AVALIDE® (irbesartan-hydrochlorothiazide) 150/12.5 mg and 300/12.5 mg tablets are peach, biconvex, and oval with a heart debossed on one side and "2775" or "2776" on the reverse side. The 300/25 mg film-coated tablet is pink, biconvex, and oval with a heart debossed on one side and "2788" on the reverse side. AVALIDE® Tablets are supplied as follows:

Irbesartan | HCTZ | NDC for | unit of use
(mg) | (mg) | Bottle of 30 | Bottle of 90
150 | 12.5 | 54868-4494-0 | --
300 | 12.5 | 54868-4526-0 | 54868-4526-1
300 | 25 | 54868-5465-0 | 54868-5465-1

16.2 Storage

Store at 25°C (77°F); excursions permitted to 15°C-30°C (59°F-86°F) [see USP Controlled Room Temperature].

17 PATIENT COUNSELING INFORMATION

Enter section text here

17.1 Pregnancy

Female patients of childbearing age should be told that use of drugs like AVALIDE during the second or third trimesters of pregnancy can cause serious problems in the fetus and infant including: low blood pressure, poor development of skull bones, kidney failure, and death. These effects have not occurred with drug exposure limited to the first trimester. Women using AVALIDE who become pregnant should notify their physician as soon as possible.

17.2 Symptomatic Hypotension

Patients using AVALIDE should be told that they may feel lightheaded, especially during the first days of use. Patients should inform their physician if they feel lightheaded or faint. If fainting occurs, the patient should stop using AVALIDE and contact the prescribing doctor.

Patients using AVALIDE should be told that getting dehydrated can lower their blood pressure too much and lead to lightheadedness and possible fainting. Dehydration may occur with excessive sweating, diarrhea, or vomiting and with not drinking enough liquids.

Manufactured by:
Bristol-Myers Squibb Company
Princeton, New Jersey 08543 USA

Distributed by:
Bristol-Myers Squibb Sanofi-Synthelabo Partnership
New York, New York 10016

1243926A1
Rev November 2008

Relabeling of "Additional Barcode Label" by:

Physicians Total Care, Inc.
Tulsa, OK 74146

PRINCIPAL DISPLAY PANEL

AVALIDE® (irbesartan-hydrochlorothiazide)

150/12.5 mg

AVALIDE® (irbesartan-hydrochlorothiazide)

300/12.5 mg

AVALIDE® (irbesartan-hydrochlorothiazide)

300/25 mg